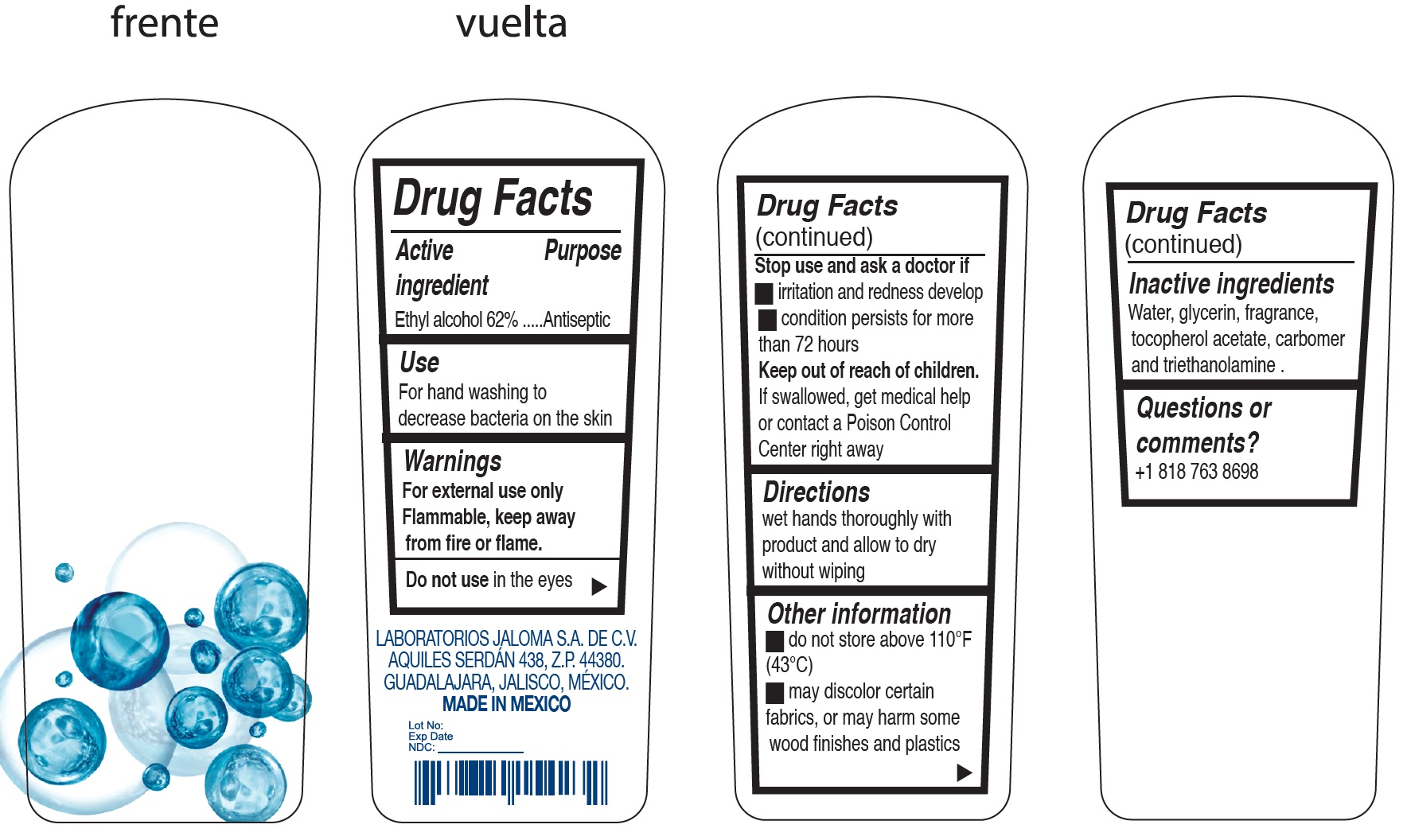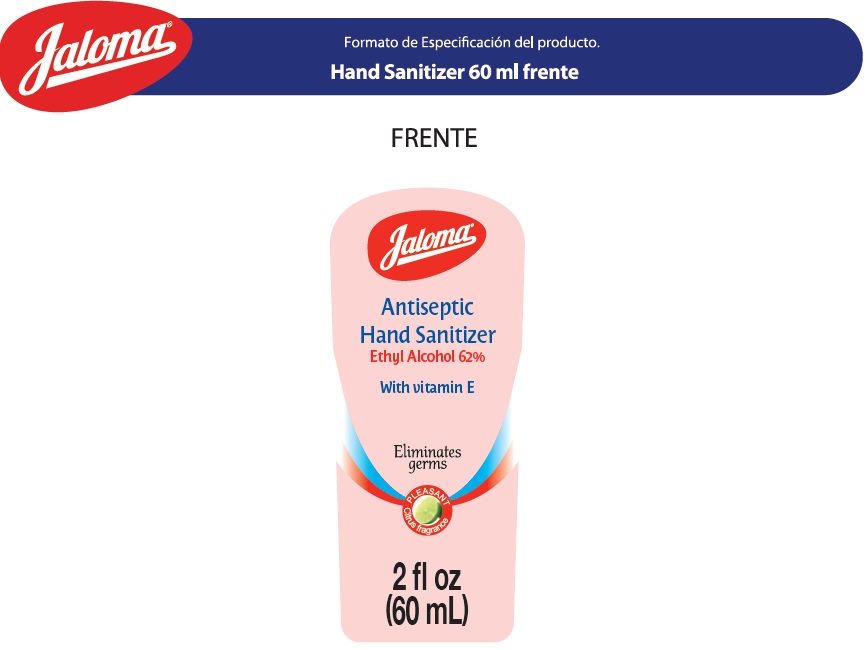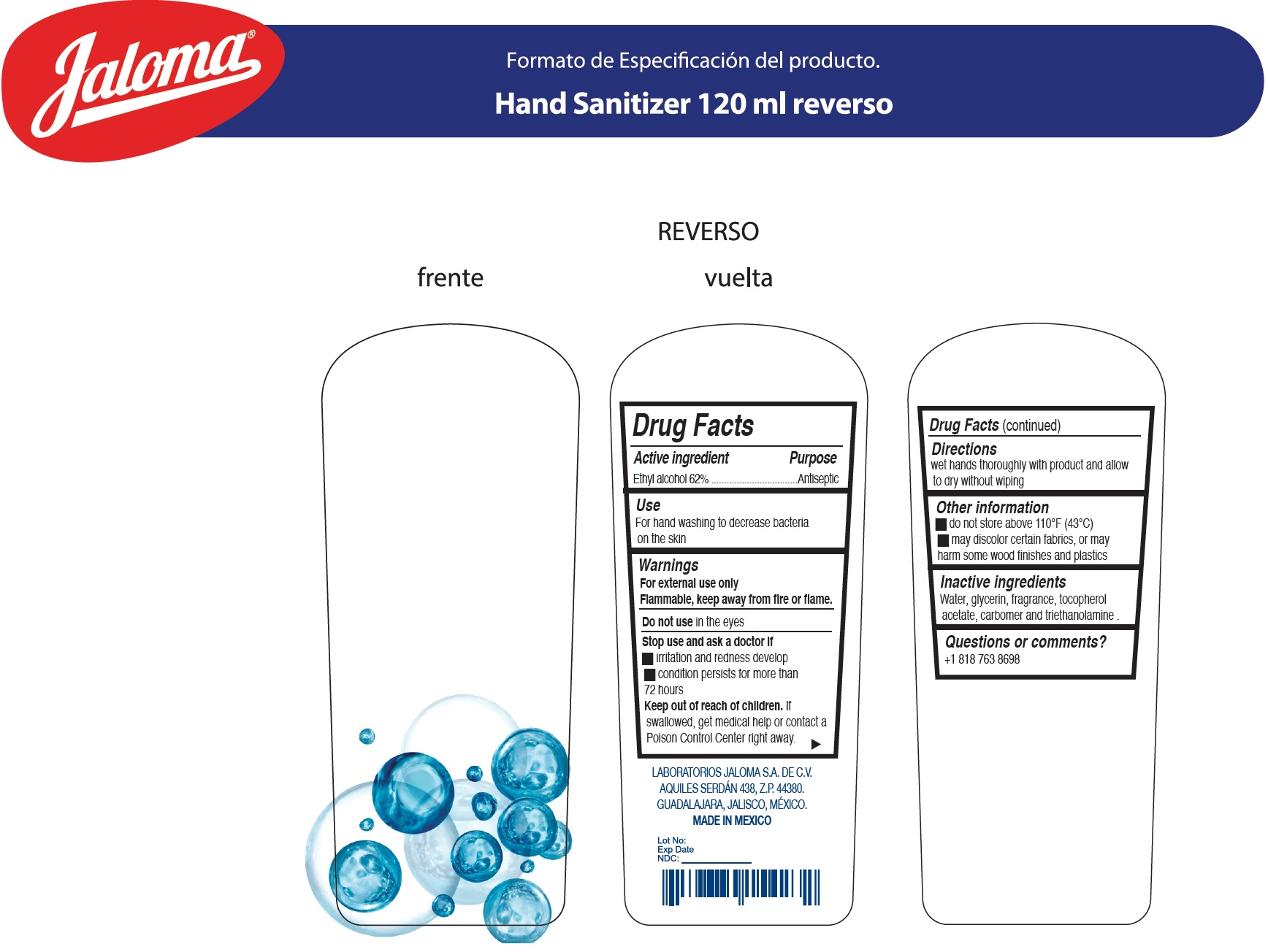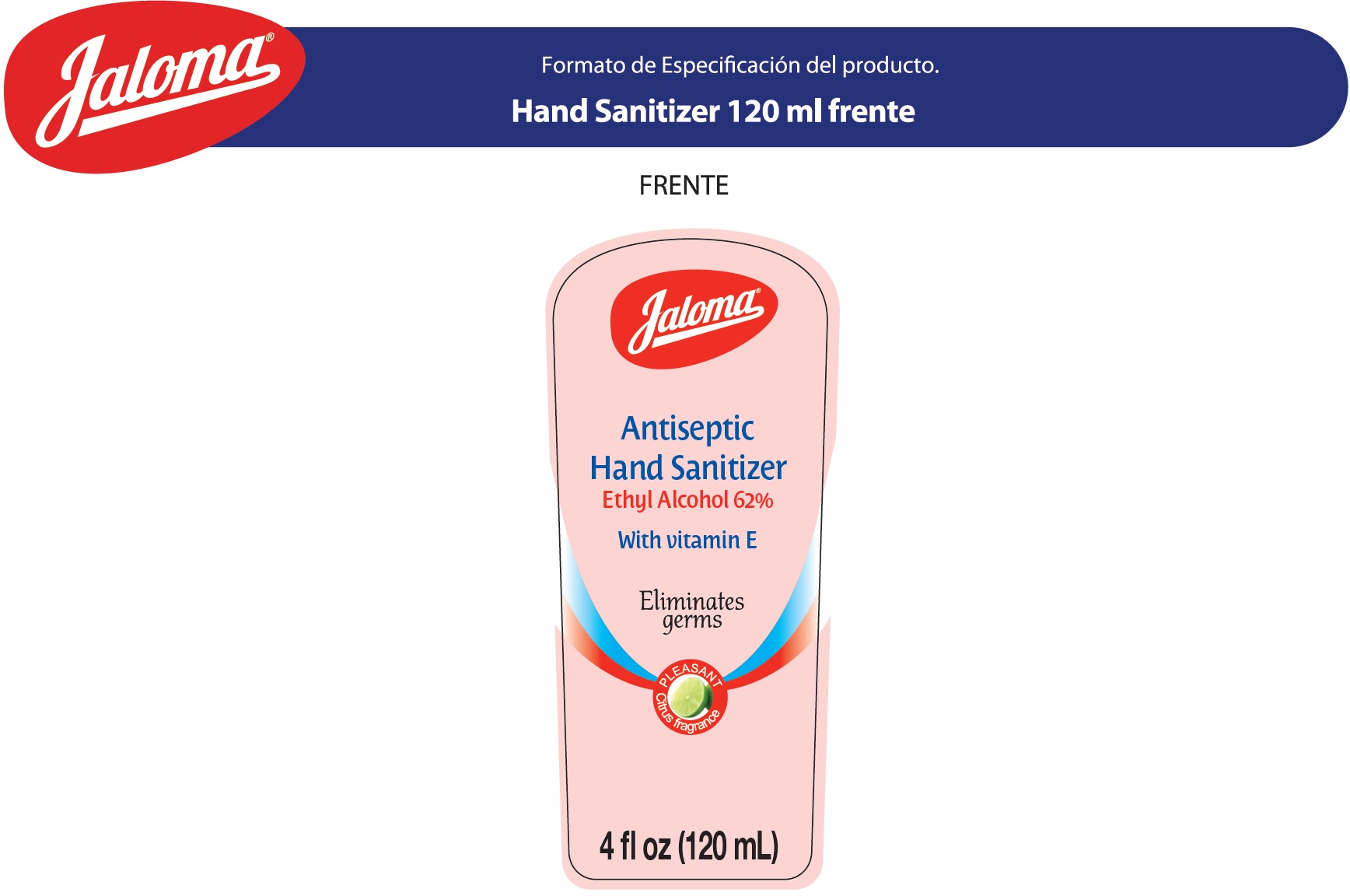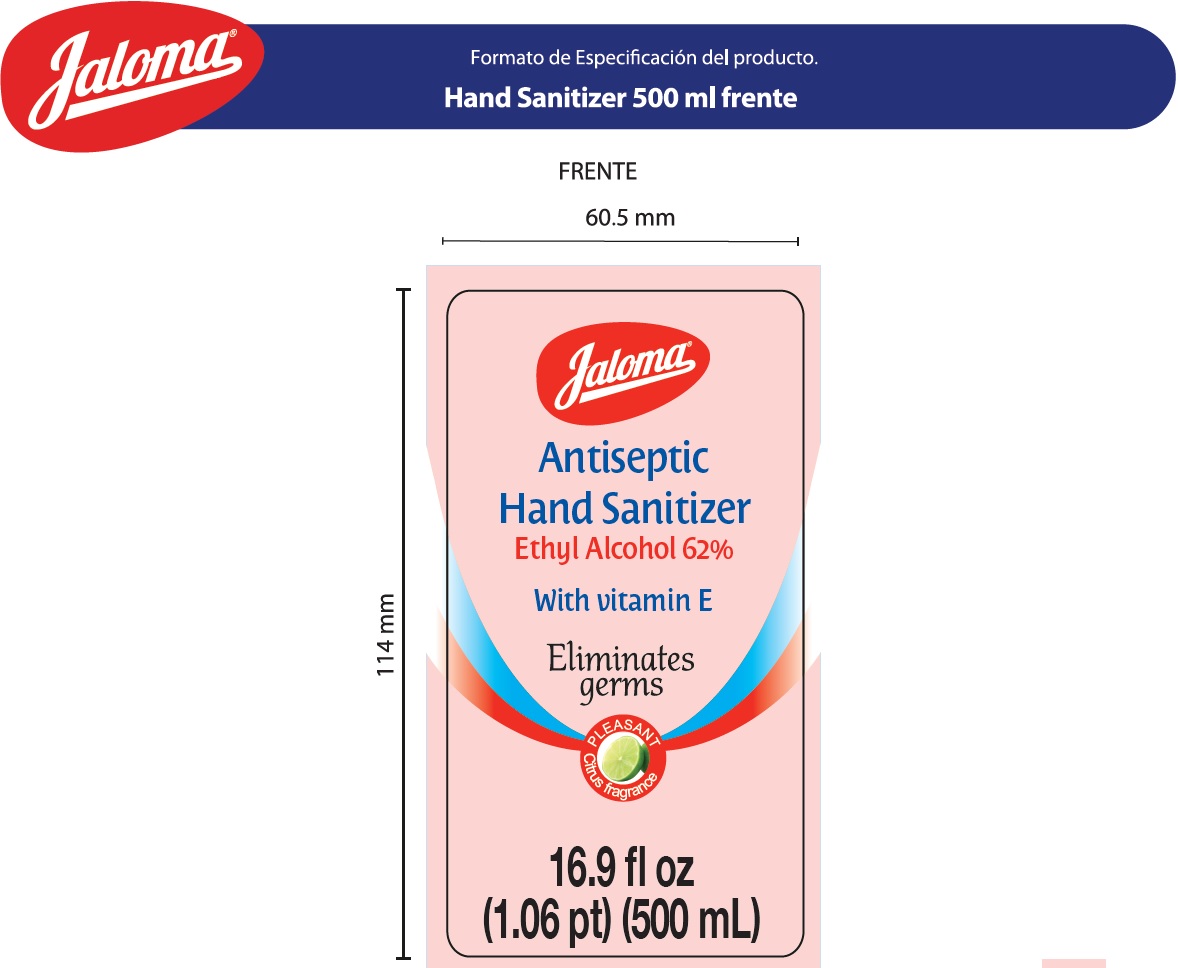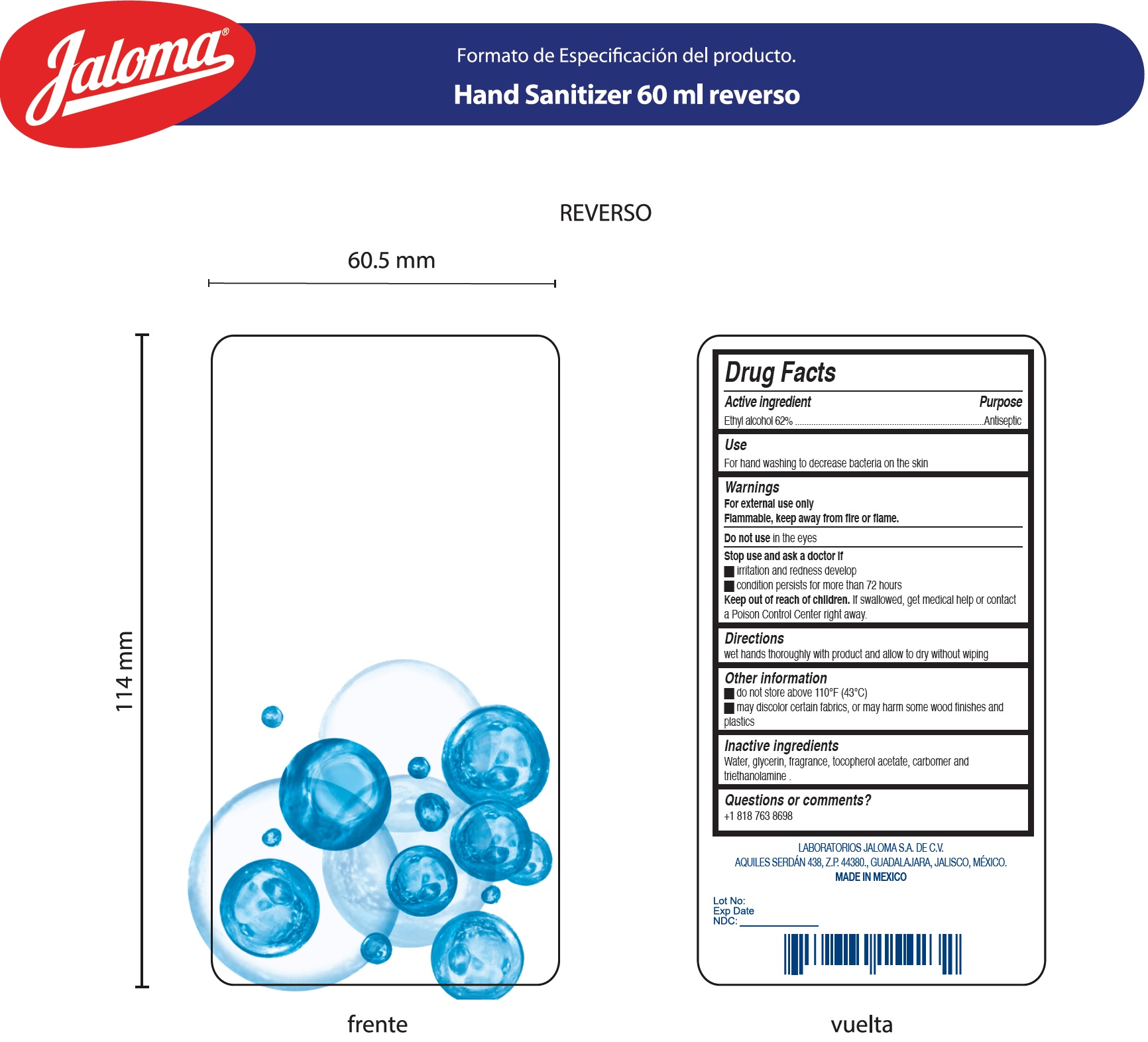 DRUG LABEL: Antiseptic Hand Sanitizer
NDC: 65055-600 | Form: GEL
Manufacturer: Laboratorios Jaloma S.A. de C.V.
Category: otc | Type: HUMAN OTC DRUG LABEL
Date: 20200327

ACTIVE INGREDIENTS: ALCOHOL 0.62 mL/1 mL
INACTIVE INGREDIENTS: WATER; GLYCERIN; .ALPHA.-TOCOPHEROL ACETATE; CARBOMER HOMOPOLYMER, UNSPECIFIED TYPE; TROLAMINE

Antiseptic Hand Sanitizer

Active ingredient

Ethyl alcohol 62%

Purpose

Antiseptic

Use

For hand washing to decrease bacteria on the skin

Warnings

For external use only
Flammable, keep away from fire or flame.

Do not use

in the eyes

Stop use and ask a doctor if

- irritation and redness develop
- condition persists for more than 72 hours

Keep out of reach of children.

If swallowed, get medical help or contact a Poison Control Center right away

Directions

wet hands thoroughly with product and allow to dry without wiping

Other information

- do not store above 110°F (43°C)
- may discolor certain fabrics, or may harm some wood finishes and plastics

Inactive ingredients

Water, glycerin, fragrance, tocopherol acetate, carbomer and triethanolamine.

Questions or comments?

+1 818 763 8698